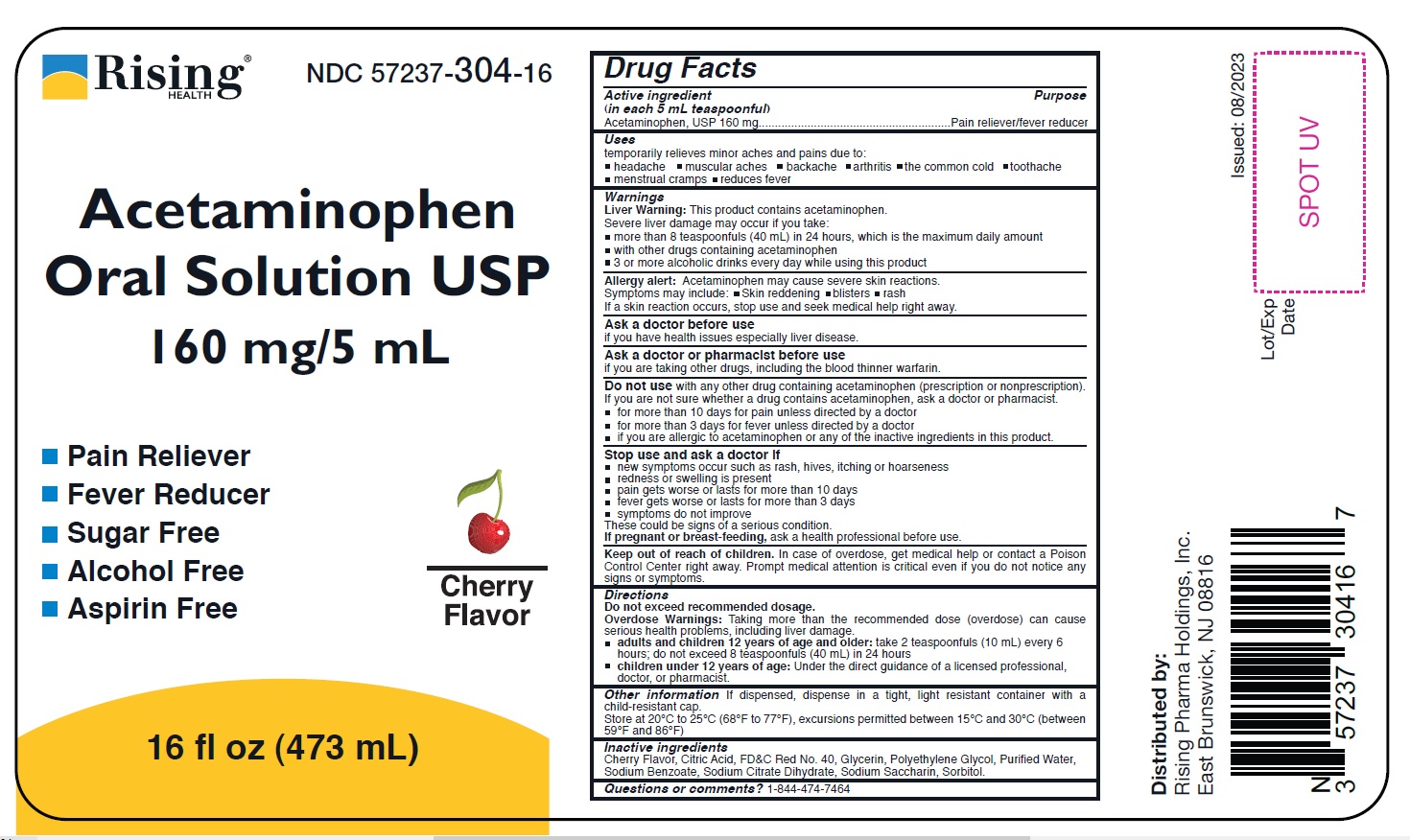 DRUG LABEL: Acetaminophen
NDC: 57237-304 | Form: SOLUTION
Manufacturer: Rising Pharma Holdings, Inc.
Category: otc | Type: HUMAN OTC DRUG LABEL
Date: 20241017

ACTIVE INGREDIENTS: ACETAMINOPHEN 160 mg/5 mL
INACTIVE INGREDIENTS: ANHYDROUS CITRIC ACID; FD&C RED NO. 40; POLYETHYLENE GLYCOL, UNSPECIFIED; WATER; SODIUM BENZOATE; TRISODIUM CITRATE DIHYDRATE; SACCHARIN SODIUM; SORBITOL; GLYCERIN

Acetaminophen Oral Solution USP, 160 mg/5 mL

Drug Facts

Active ingredient (in each 5 mL teaspoonful)

Acetaminophen, USP 160 mg

Purpose

Pain reliever/fever reducer

Uses

temporarily relieves minor aches and pains due to:

- headache
- muscular aches
- backache
- arthritis
- the common cold
- toothache
- menstrual cramps
- reduces fever

Warnings

Liver Warning: This product contains acetaminophen.

Severe liver damage may occur if you take:

- more than 8 teaspoonfuls (40 mL) in 24 hours, which is the maximum daily amount
- with other drugs containing acetaminophen
- 3 or more alcoholic drinks every day while using this product

Allergy alert

Acetaminophen may cause severe skin reactions.

Symptoms may include:

- skin reddening
- blisters
- rash

If a skin reaction occurs, stop use and seek medical help right away.

Ask a doctor before use

if you have health issues especially liver disease.

Ask a doctor or pharmacist before use

if you are taking other drugs, including the blood thinner warfarin.

Do not use with any other drug containing acetaminophen (prescription or nonprescription). If you are not sure whether a drug contains acetaminophen, ask a doctor or pharmacist.

- for more than 10 days for pain unless directed by a doctor
- for more than 3 days for fever unless directed by a doctor
- if you are allergic to acetaminophen or any of the inactive ingredients in this product.

Stop use and ask a doctor if

- new symptoms occur such as rash, hives, itching or hoarseness
- redness or swelling is present
- pain gets worse or lasts for more than 10 days
- fever gets worse or lasts for more than 3 days
- symptoms do not improve

These could be signs of a serious condition.

PREGNANCY OR BREAST FEEDING

If pregnant or breast-feeding, ask a health professional before use.

Keep out of reach of children. In case of overdose, get medical help or contact a Poison Control Center right away. Prompt medical attention is critical even if you do not notice any signs or symptoms.

Directions

Do not exceed recommended dosage.

Overdose Warnings: Taking more than the recommended dose (overdose) can cause serious health problems, including liver damage.

- adults and children 12 years of age and older: take 2 teaspoonfuls (10 mL) every 6 hours; do not exceed 8 teaspoonfuls (40 mL) in 24 hours
- children under 12 years of age: Under the direct guidance of a licensed professional, doctor, or pharmacist.

Other information

If dispensed, dispense in a tight, light resistant container with a child-resistant cap.

Store at 20°C to 25°C (68°F to 77°F), excursions permitted between 15°C and 30°C (between 59°F and 86°F)

Inactive ingredients

Cherry Flavor, Citric Acid, FD&C Red No. 40, Glycerin, Polyethylene Glycol, Purified Water, Sodium Benzoate, Sodium Citrate Dihydrate, Sodium Saccharin, Sorbitol.

Questions or comments?

1-844-474-7464

Distributed by:

Rising Pharma Holdings, Inc.

East Brunswick, NJ 08816

Issued:08/2023

PRINCIPAL DISPLAY PANEL - 473 mL Bottle Label

NDC 57237-304-16

Acetaminophen Oral Solution USP
160 mg/5 mL

Pain Reliever

Fever Reducer

Sugar Free

Alcohol Free

Aspirin Free

Cherry Flavor

16 fl. oz. (473 mL)